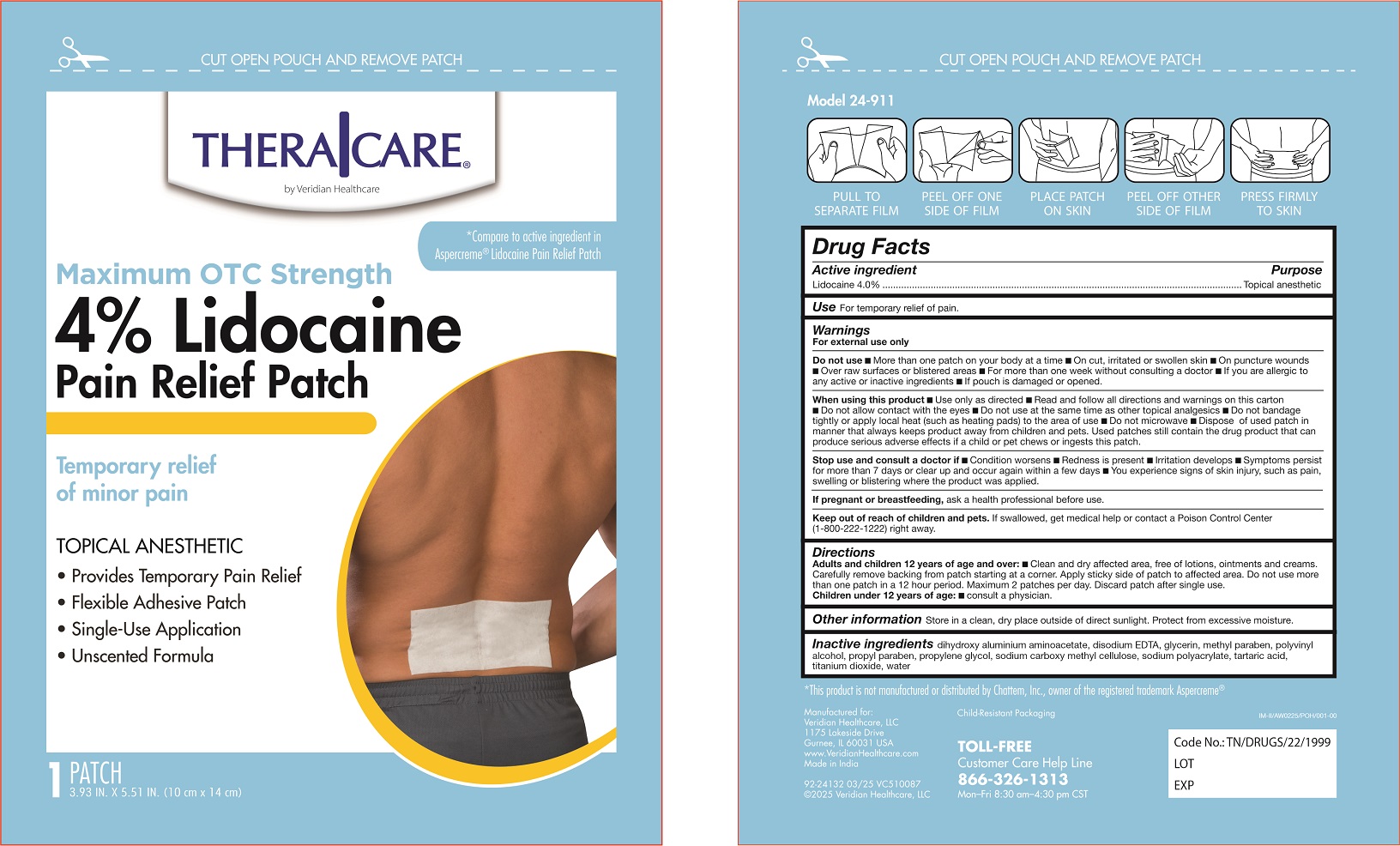 DRUG LABEL: Maximum Strength 4% Lidocaine Patch
NDC: 71811-004 | Form: PATCH
Manufacturer: InterMed Laboratories Private Limited
Category: otc | Type: HUMAN OTC DRUG LABEL
Date: 20250429

ACTIVE INGREDIENTS: LIDOCAINE 40 mg/1 1
INACTIVE INGREDIENTS: CARBOXYMETHYLCELLULOSE CALCIUM; TARTARIC ACID; TITANIUM DIOXIDE; CARBOXYMETHYLCELLULOSE SODIUM; DIHYDROXYALUMINUM AMINOACETATE; GLYCERIN; EDETATE DISODIUM ANHYDROUS; METHYLPARABEN; SODIUM POLYACRYLATE (2500000 MW); PROPYLENE GLYCOL; POLYVINYL ALCOHOL, UNSPECIFIED; PROPYLPARABEN; WATER

Maximum Strength 4% Lidocaine Patch

Active Ingredient

Lidocaine 4%

Purpose

Topical Anesthetic

Uses

Temporarily relieves minor pain

Warnings

For external use only

Do Not Use

- more than 1 patch on your body at a time or on cut, irritated or swollen skin
- on puncture wounds
- for more than one week without consulting a doctor
- over raw surfaces or blistered areas
- uif you are allergic to any active or inactive ingredients
- if pouch is damaged or opened

When Using This Product

- use only as directed. Read and follow all directions and warnings on this label.
- do not allow contact with the eyes
- do not bandage tightly or apply local heat (such as heating pads) to the area of use
- do not use at the same time as other topical analgesics
- dispose of used patch in manner that always keeps product away from children or pets. Used patches still contain the drug product that can produce serious adverse effects if a child or pet chews or ingests this patch.

Stop Use and Ask a Doctor if

- condition worsens
- redness is present
- irritation develops
- symptoms persist for more than 7 days or clear up and occur again within a few days
- you experience signs of skin injury, such as pain, swelling, or blistering where the product was applied

If Pregnant or Breast Feeding

ask a health professional before use.

Keep Out of Reach of Children and Pets

If swallowed, get medical help or contact a Poison Control Center right away.

Directions

Adults and children over 12 years:

- clean and dry affected area free of lotions, ointments and creams.
- carefully remove backing from patch starting at a corner. Apply sticky side of patch ti affected area.
- Do not use more than one patch in a 12 hour period. Maximum 2 patches per day. Discar patch after single use.

children 12 years or younger:ask a physician.

Directions

Adults and children over 12 years:

- clean and dry affected area
- remove backing from patch by firmly grasping both ends and gently pulling until backing separates in middle
- carefully remove smaller portion of backing from patch and apply exposed portion of patch to affected area
- once exposed portion of patch is positioned, carefully remove remaining backing to completely apply patch to affected area
- use 1 patch for up to 12 hours

children 12 years or younger:ask a doctor

Inactive Ingredients

dihydroxy aluminium aminoacetate, disodium EDTA, glycerin, methyl paraben, polyvinyl alcohol, propyl paraben, propylene glycol, sodium carboxy methyl cellulose, sodium polyacrylate, tartaric acid, titanium dioxide, water